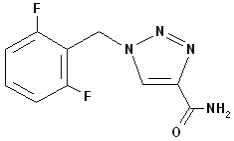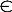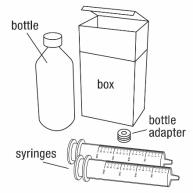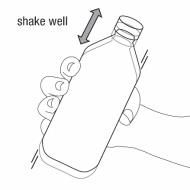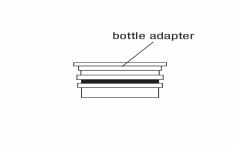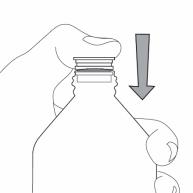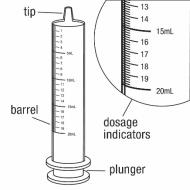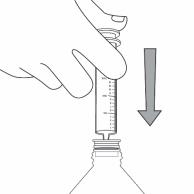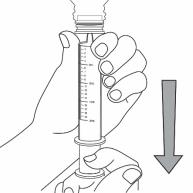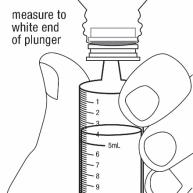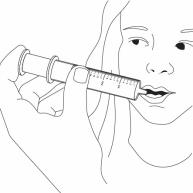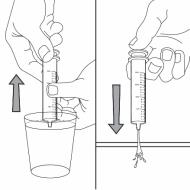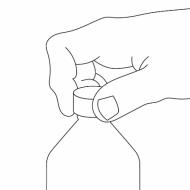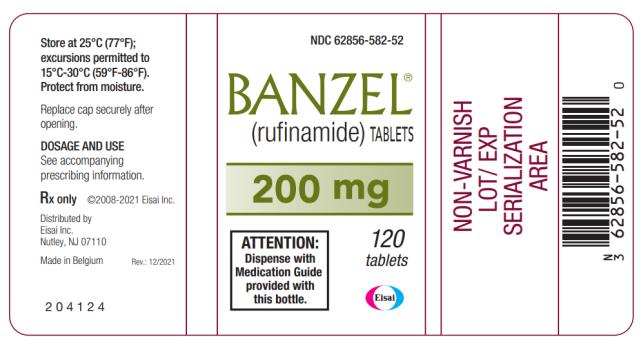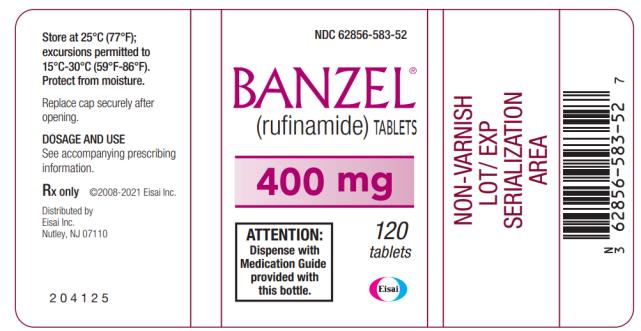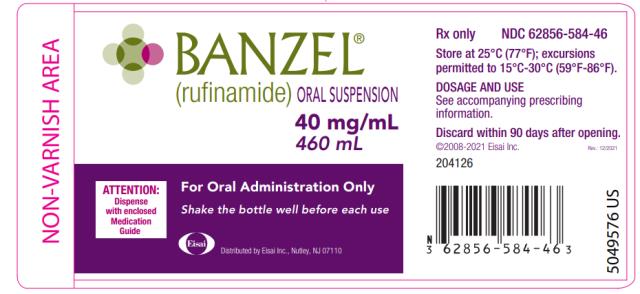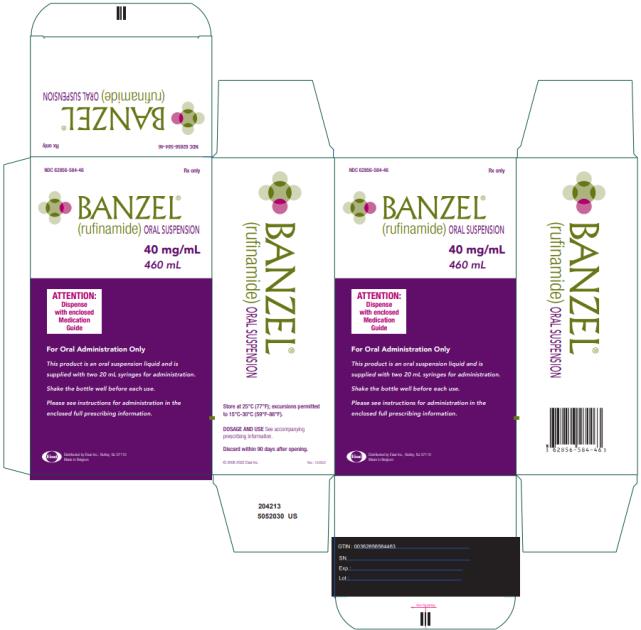 DRUG LABEL: Banzel
NDC: 62856-582 | Form: TABLET, FILM COATED
Manufacturer: Eisai Inc.
Category: prescription | Type: HUMAN PRESCRIPTION DRUG LABEL
Date: 20221215

ACTIVE INGREDIENTS: RUFINAMIDE 200 mg/1 1
INACTIVE INGREDIENTS: SILICON DIOXIDE; STARCH, CORN; CROSCARMELLOSE SODIUM; HYPROMELLOSE 2208 (3 MPA.S); LACTOSE MONOHYDRATE; MAGNESIUM STEARATE; CELLULOSE, MICROCRYSTALLINE; SODIUM LAURYL SULFATE; HYPROMELLOSE 2910 (3 MPA.S); FERRIC OXIDE RED; POLYETHYLENE GLYCOL 8000; TALC; TITANIUM DIOXIDE

HIGHLIGHTS OF PRESCRIBING INFORMATION

These highlights do not include all the information needed to use BANZEL® safely and effectively. See full prescribing information for BANZEL®.
BANZEL® (rufinamide) film-coated tablet, for oral use
BANZEL® (rufinamide) oral suspension
Initial U.S. Approval: 2008

1 INDICATIONS AND USAGE

BANZEL is indicated for adjunctive treatment of seizures associated with Lennox-Gastaut Syndrome (LGS) in pediatric patients 1 year of age and older, and in adults (1)

2 DOSAGE AND ADMINISTRATION

- BANZEL should be given with food. Tablets can be administered whole, as half tablets, or crushed (2.2)
- Measure oral suspension using provided adapter and dosing syringe (2.2)

Pediatric patients 1 year and older:

- Starting daily dose: 10 mg/kg per day in two equally divided doses (2.1)
- Increase by 10 mg/kg increments every other day to maximum dose of 45 mg/kg per day, not to exceed 3200 mg per day, in two divided doses (2.1)

Adults:

- Starting daily dose: 400-800 mg per day in two equally divided doses (2.1)
- Increase by 400-800 mg every other day until a maximum dose of 3200 mg per day, in two divided doses, is reached (2.1)

3 DOSAGE FORMS AND STRENGTHS

- Film-coated tablets: 200 mg (pink), 400 mg (pink) (3)
- Oral suspension: 40 mg/mL (3)

4 CONTRAINDICATIONS

BANZEL is contraindicated in patients with Familial Short QT syndrome (4)

5 WARNINGS AND PRECAUTIONS

- Monitor patients for new or worsening depression, suicidal thoughts/behavior, and unusual changes in mood or behavior (5.1)
- Central nervous system reactions can occur (5.2)
- Use caution when administering BANZEL with other drugs that shorten the QT interval (5.3)
- Discontinue BANZEL if multi-organ hypersensitivity reaction occurs (5.4)
- Withdraw BANZEL gradually to minimize the risk of precipitating seizures, seizure exacerbation, or status epilepticus (5.5)

6 ADVERSE REACTIONS

Most common adverse reactions (≥ 10% and greater than placebo) were headache, dizziness, fatigue, somnolence, and nausea (6.1)

To report SUSPECTED ADVERSE REACTIONS, contact Eisai Inc. at 1-888-274-2378 or www.banzel.com or FDA at 1-800-FDA-1088 or www.fda.gov/medwatch.

7 DRUG INTERACTIONS

- Patients on valproate should begin at a BANZEL dose lower than 10 mg/kg per day (pediatric patients) or 400 mg per day (adults) (7.2)
- Hormonal contraceptives may be less effective with BANZEL; use additional non-hormonal forms of contraception (7.3)

8 USE IN SPECIFIC POPULATIONS

- Pregnancy: Based on animal data, may cause fetal harm. (8.1)
- Renal impairment: Consider adjusting the BANZEL dose for the loss of drug upon dialysis (8.6)
- Not recommended in patients with severe hepatic impairment (8.7)

FULL PRESCRIBING INFORMATION

1 INDICATIONS AND USAGE

BANZEL is indicated for adjunctive treatment of seizures associated with Lennox-Gastaut Syndrome in pediatric patients 1 year of age and older and in adults.

2 DOSAGE AND ADMINISTRATION

2.1 Dosage Information

Pediatric patients (1 year to less than 17 years)

The recommended starting daily dose of BANZEL in pediatric patients with Lennox-Gastaut Syndrome is approximately 10 mg/kg administered in two equally divided doses. The dose should be increased by approximately 10 mg/kg increments every other day until a maximum daily dose of 45 mg/kg, not to exceed 3200 mg, administered in two equally divided doses, is reached. It is not known whether doses lower than the target doses are effective.

Adults (17 years and older)

The recommended starting daily dose of BANZEL in adults with Lennox-Gastaut Syndrome is 400 to 800 mg per day administered in two equally divided doses. The dose should be increased by 400-800 mg every other day until a maximum daily dose of 3200 mg, administered in two equally divided doses, is reached. It is not known whether doses lower than 3200 mg are effective.

2.2 Administration Information

Administer BANZEL with food. BANZEL film-coated tablets can be administered whole, as half tablets or crushed.

BANZEL oral suspension should be shaken well before every administration. The provided adapter and calibrated oral dosing syringe should be used to administer the oral suspension. The adapter which is supplied in the product carton should be inserted firmly into the neck of the bottle before use and remain in place for the duration of the usage of the bottle. The dosing syringe should be inserted into the adapter and the dose withdrawn from the inverted bottle. The cap should be replaced after each use. The cap fits properly when the adapter is in place [see Patient Counseling Information (17)].

2.3 Dosing in Patients Undergoing Hemodialysis

Hemodialysis may reduce exposure to a limited (about 30%) extent. Accordingly, adjusting the BANZEL dose during the dialysis process should be considered [see Clinical Pharmacology (12.3)].

2.4 Dosing in Patients with Hepatic Disease

Use of BANZEL in patients with hepatic impairment has not been studied. Therefore, use in patients with severe hepatic impairment is not recommended. Caution should be exercised in treating patients with mild to moderate hepatic impairment [see Use in Specific Populations (8.7)].

2.5 Dosing in Patients Taking Valproate

Patients taking valproate should begin BANZEL at a dose lower than 10 mg/kg per day in pediatric patients or 400 mg per day in adults [see Drug Interactions (7.2)].

3 DOSAGE FORMS AND STRENGTHS

Film-coated Tablets: 200 mg (pink) and 400 mg (pink). Tablets are scored on both sides.

Oral Suspension: 40 mg/mL. White to off-white opaque liquid.

4 CONTRAINDICATIONS

BANZEL is contraindicated in patients with Familial Short QT syndrome [see Warnings and Precautions (5.3)].

5 WARNINGS AND PRECAUTIONS

5.1 Suicidal Behavior and Ideation

Antiepileptic drugs (AEDs), including BANZEL, increase the risk of suicidal thoughts or behavior in patients taking these drugs for any indication. Patients treated with any AED for any indication should be monitored for the emergence or worsening of depression, suicidal thoughts or behavior, and/or any unusual changes in mood or behavior.

Pooled analyses of 199 placebo-controlled clinical trials (mono- and adjunctive therapy) of 11 different AEDs showed that patients randomized to one of the AEDs had approximately twice the risk (adjusted Relative Risk 1.8, 95% CI:1.2, 2.7) of suicidal thinking or behavior compared to patients randomized to placebo. In these trials, which had a median treatment duration of 12 weeks, the estimated incidence rate of suicidal behavior or ideation among 27,863 AED-treated patients was 0.43%, compared to 0.24% among 16,029 placebo-treated patients, representing an increase of approximately one case of suicidal thinking or behavior for every 530 patients treated. There were four suicides in drug-treated patients in the trials and none in placebo-treated patients, but the number is too small to allow any conclusion about drug effect on suicide.

The increased risk of suicidal thoughts or behavior with AEDs was observed as early as 1 week after starting drug treatment with AEDs and persisted for the duration of treatment assessed. Because most trials included in the analysis did not extend beyond 24 weeks, the risk of suicidal thoughts or behavior beyond 24 weeks could not be assessed.

The risk of suicidal thoughts or behavior was generally consistent among drugs in the data analyzed. The finding of increased risk with AEDs of varying mechanisms of action and across a range of indications suggests that the risk applies to all AEDs used for any indication. The risk did not vary substantially by age (5-100 years) in the clinical trials analyzed. Table 1 shows absolute and relative risk by indication for all evaluated AEDs.

Table 1: Absolute and Relative Risk of Suicidal Behavior and Ideation
Indication | Placebo Patients with Events Per 1000 Patients | Drug Patients with Events Per 1000 Patients | Relative Risk: Incidence of Events in Drug Patients/Incidence in Placebo Patients | Risk Difference: Additional Drug Patients with Events Per 1000 Patients
Epilepsy | 1.0 | 3.4 | 3.5 | 2.4
Psychiatric | 5.7 | 8.5 | 1.5 | 2.9
Other | 1.0 | 1.8 | 1.9 | 0.9
Total | 2.4 | 4.3 | 1.8 | 1.9

The relative risk for suicidal thoughts or behavior was higher in clinical trials for epilepsy than in clinical trials for psychiatric or other conditions, but the absolute risk differences were similar for the epilepsy and psychiatric indications.

Anyone considering prescribing BANZEL or any other AED must balance the risk of suicidal thoughts or behavior with the risk of untreated illness. Epilepsy and many other illnesses for which AEDs are prescribed are themselves associated with morbidity and mortality and an increased risk of suicidal thoughts and behavior. Should suicidal thoughts and behavior emerge during treatment, consider whether the emergence of these symptoms in any given patient may be related to the illness being treated.

5.2 Central Nervous System Reactions

Use of BANZEL has been associated with central nervous system-related adverse reactions in the controlled clinical trial of patients 4 years or older with Lennox-Gastaut Syndrome. The most significant of these can be classified into two general categories: 1) somnolence or fatigue, and 2) coordination abnormalities, dizziness, gait disturbances, and ataxia.

Somnolence was reported in 24% of BANZEL-treated patients compared to 13% of patients on placebo, and led to study discontinuation in 3% of BANZEL-treated patients compared to 0% of patients on placebo. Fatigue was reported in 10% of BANZEL-treated patients compared to 8% of patients on placebo. It led to study discontinuation in 1% of BANZEL-treated patients and 0% of patients on placebo.

Dizziness was reported in 2.7% of BANZEL-treated patients compared to 0% of patients on placebo, and did not lead to study discontinuation.

Ataxia and gait disturbance were reported in 5.4% and 1.4% of BANZEL-treated patients, respectively, compared to no patient on placebo. None of these reactions led to study discontinuation.

Accordingly, patients should be advised not to drive or operate machinery until they have gained sufficient experience on BANZEL to gauge whether it adversely affects their ability to drive or operate machinery.

5.3 QT Shortening

Formal cardiac ECG studies demonstrated shortening of the QT interval (mean = 20 msec, for doses >2400 mg twice daily) with BANZEL. In a placebo-controlled study of the QT interval, a higher percentage of BANZEL-treated subjects (46% at 2400 mg, 46% at 3200 mg, and 65% at 4800 mg) had a QT shortening of greater than 20 msec at Tmax compared to placebo (5-10%).

Reductions of the QT interval below 300 msec were not observed in the formal QT studies with doses up to 7200 mg per day. Moreover, there was no signal for drug-induced sudden death or ventricular arrhythmias.

The degree of QT shortening induced by BANZEL is without any known clinical risk. Familial Short QT syndrome is associated with an increased risk of sudden death and ventricular arrhythmias, particularly ventricular fibrillation. Such events in this syndrome are believed to occur primarily when the corrected QT interval falls below 300 msec. Non-clinical data also indicate that QT shortening is associated with ventricular fibrillation.

Patients with Familial Short QT syndrome should not be treated with BANZEL. Caution should be used when administering BANZEL with other drugs that shorten the QT interval [see Contraindications (4)].

5.4 Multi-organ Hypersensitivity/Drug Reaction with Eosinophilia and Systemic Symptoms (DRESS)

Drug Reaction with Eosinophilia and Systemic Symptoms (DRESS), also known as multi-organ hypersensitivity, has been reported in patients taking antiepileptic drugs, including BANZEL. DRESS may be fatal or life-threatening. DRESS typically, although not exclusively, presents with fever, rash, and/or lymphadenopathy, and/or facial swelling, in association with other organ system involvement, such as hepatitis, nephritis, hematological abnormalities, myocarditis, or myositis, sometimes resembling an acute viral infection. Eosinophilia is often present. It is important to note that early manifestations of hypersensitivity, such as fever or lymphadenopathy, may be present even though rash is not evident. Because this disorder is variable in its expression, other organ systems not noted here may be involved.

All cases of DRESS identified in clinical trials with BANZEL occurred in pediatric patients less than 12 years of age, occurred within 4 weeks of treatment initiation, and resolved or improved with BANZEL discontinuation. DRESS has also been reported in adult and pediatric patients taking BANZEL in the postmarketing setting.

If DRESS is suspected, the patient should be evaluated immediately, BANZEL should be discontinued, and alternative treatment should be started.

5.5 Withdrawal of AEDs

As with all antiepileptic drugs, BANZEL should be withdrawn gradually to minimize the risk of precipitating seizures, seizure exacerbation, or status epilepticus. If abrupt discontinuation of the drug is medically necessary, the transition to another AED should be made under close medical supervision. In clinical trials, BANZEL discontinuation was achieved by reducing the dose by approximately 25% every 2 days.

5.6 Status Epilepticus

Estimates of the incidence of treatment emergent status epilepticus among patients treated with BANZEL are difficult because standard definitions were not employed. In a controlled Lennox-Gastaut Syndrome trial, 3 of 74 (4.1%) BANZEL-treated patients had episodes that could be described as status epilepticus in the BANZEL-treated patients compared with none of the 64 patients in the placebo-treated patients. In all controlled trials that included patients with different epilepsies, 11 of 1240 (0.9%) BANZEL-treated patients had episodes that could be described as status epilepticus compared with none of 635 patients in the placebo-treated patients.

5.7 Leukopenia

BANZEL has been shown to reduce white cell count. Leukopenia (white cell count < 3X10^9 L) was more commonly observed in BANZEL-treated patients 43 of 1171 (3.7%) than placebo-treated patients, 7 of 579 (1.2%) in all controlled trials.

6 ADVERSE REACTIONS

The following serious adverse reactions are described below and elsewhere in the labeling:

- Suicidal Behavior and Ideation [see Warnings and Precautions (5.1)]
- Central Nervous System Reactions [see Warnings and Precautions (5.2)]
- QT Shortening [see Warnings and Precautions (5.3)]
- Multi-Organ Hypersensitivity/Drug Reaction with Eosinophilia and Systemic Symptoms (DRESS) [see Warnings and Precautions (5.4)]
- Leukopenia [see Warnings and Precautions (5.7)]

6.1 Clinical Trials Experience

Because clinical trials are conducted under widely varying conditions, adverse reaction rates observed in the clinical trials of a drug cannot be directly compared to rates in the clinical trials of another drug and may not reflect the rates observed in practice.

Adverse Reactions in Adult and Pediatric Patients ages 3 to 17 years of age

In the pooled, double-blind, adjunctive therapy studies in adult and pediatric patients ages 3 to 17 years of age, the most common (≥10%) adverse reactions in BANZEL-treated patients, in all doses studied (200 to 3200 mg per day) with a higher frequency than in patients on placebo were: headache, dizziness, fatigue, somnolence, and nausea.

Table 2 lists adverse reactions that occurred in at least 3% of pediatric patients (ages 3 to less than 17 years) with epilepsy treated with BANZEL in controlled adjunctive studies and were numerically more common in patients treated with BANZEL than in patients on placebo.

At the target dose of 45 mg/kg per day for adjunctive therapy in pediatric patients (ages 3 to less than 17 years), the most common (≥3%) adverse reactions with an incidence greater than in placebo for BANZEL were somnolence, vomiting, and headache.

Table 2: Adverse Reactions in Pediatric Patients (Ages 3 to less than 17 years) in Pooled Double-Blind Adjunctive Trials
Adverse Reaction | BANZEL (N=187) % | Placebo (N=182) %
Somnolence | 17 | 9
Vomiting | 17 | 7
Headache | 16 | 8
Fatigue | 9 | 8
Dizziness | 8 | 6
Nausea | 7 | 3
Influenza | 5 | 4
Nasopharyngitis | 5 | 3
Decreased Appetite | 5 | 2
Rash | 4 | 2
Ataxia | 4 | 1
Diplopia | 4 | 1
Bronchitis | 3 | 2
Sinusitis | 3 | 2
Psychomotor Hyperactivity | 3 | 1
Upper Abdominal Pain | 3 | 2
Aggression | 3 | 2
Ear Infection | 3 | 1
Disturbance in Attention | 3 | 1
Pruritis | 3 | 0

Table 3 lists adverse reactions that occurred in at least 3% of adult patients with epilepsy treated with BANZEL (up to 3200 mg per day) in adjunctive controlled studies and were numerically more common in patients treated with BANZEL than in patients on placebo. In these studies, either BANZEL or placebo was added to the current AED therapy.

At all doses studied of up to 3200 mg per day given as adjunctive therapy in adults, the most common (≥ 3%) adverse reactions, and with the greatest increase in incidence compared to placebo, for BANZEL were dizziness, fatigue, nausea, diplopia, vision blurred, and ataxia.

Table 3: Adverse Reactions in Adults in Pooled Double-Blind Adjunctive Trials
Adverse Reaction | BANZEL (N=823) % | Placebo (N=376) %
Headache | 27 | 26
Dizziness | 19 | 12
Fatigue | 16 | 10
Nausea | 12 | 9
Somnolence | 11 | 9
Diplopia | 9 | 3
Tremor | 6 | 5
Nystagmus | 6 | 5
Blurred Vision | 6 | 2
Vomiting | 5 | 4
Ataxia | 4 | 0
Upper Abdominal Pain | 3 | 2
Anxiety | 3 | 2
Constipation | 3 | 2
Dyspepsia | 3 | 2
Back Pain | 3 | 1
Gait Disturbance | 3 | 1
Vertigo | 3 | 1

Discontinuation in Controlled Clinical Studies

In controlled, double-blind, adjunctive clinical studies, 9% of pediatric and adult patients receiving BANZEL as adjunctive therapy and 4% receiving placebo discontinued as a result of an adverse reaction. The adverse reactions most commonly leading to discontinuation of BANZEL (>1%) used as adjunctive therapy were generally similar in adults and pediatric patients.

In pediatric patients (ages 4 to less than 17 years) double-blind adjunctive clinical studies, 8% of patients receiving BANZEL as adjunctive therapy (at the recommended dose of 45 mg/kg per day) and 2% receiving placebo discontinued as a result of an adverse reaction. The adverse reactions most commonly leading to discontinuation of BANZEL (>1%) used as adjunctive therapy are presented in Table 4.

Table 4: Most Common Adverse Reactions Leading to Discontinuation in Pediatric Patients (Ages 4 to less than 17 years) in Pooled Double-Blind Adjunctive Trials
Adverse Reaction | BANZEL (N=187) % | Placebo (N=182) %
Convulsion | 2 | 1
Rash | 2 | 1
Fatigue | 2 | 0
Vomiting | 1 | 0

In adult double-blind, adjunctive clinical studies, 10% of patients receiving BANZEL as adjunctive therapy (at doses up to 3200 mg per day) and 6% receiving placebo discontinued as a result of an adverse reaction. The adverse reactions most commonly leading to discontinuation of BANZEL (>1%) used as adjunctive therapy are presented in Table 5.

Table 5: Most Common Adverse Reactions Leading to Discontinuation in Adult Patients in Pooled Double-Blind Adjunctive Trials
Adverse Reaction | BANZEL (N=823) % | Placebo (N=376) %
Dizziness | 3 | 1
Fatigue | 2 | 1
Headache | 2 | 1
Nausea | 1 | 0
Ataxia | 1 | 0

Pediatric Patients ages 1 to less than 4 years

In a multicenter, parallel group, open-label study comparing BANZEL (45 mg/kg per day) adjunctive treatment (n=25) to the adjunctive treatment with an AED of the investigator’s choice (n=11) in pediatric patients (1 year to less than 4 years of age) with inadequately controlled Lennox-Gastaut Syndrome, the adverse reaction profile was generally similar to that observed in adults and pediatric patients 4 years of age and older treated with BANZEL. Adverse reactions that occurred in at least 2 (8%) BANZEL-treated patients and with a higher frequency than in the AED comparator group were: vomiting (24%), somnolence (16%), bronchitis (12%), constipation (12%), cough (12%), decreased appetite (12%), rash (12%), otitis media (8%), pneumonia (8%), decreased weight (8%), gastroenteritis (8%), nasal congestion (8%), and pneumonia aspiration (8%).

Other Adverse Reactions Observed During Clinical Trials

BANZEL has been administered to 1978 individuals during all epilepsy clinical trials (placebo-controlled and open-label). Adverse reactions occurring during these studies were recorded by the investigators using terminology of their own choosing. To provide a meaningful estimate of the proportion of patients having adverse reactions, these events were grouped into standardized categories using the MedDRA dictionary. Adverse events occurring at least three times and considered possibly related to treatment are included in the System Organ Class listings below. Terms not included in the listings are those already included in the tables above, those too general to be informative, those related to procedures, and terms describing events common in the population. Some events occurring fewer than 3 times are also included based on their medical significance. Because the reports include events observed in open-label, uncontrolled observations, the role of BANZEL in their causation cannot be reliably determined.

Events are classified by body system and listed in order of decreasing frequency as follows: frequent adverse events—those occurring in at least 1/100 patients; infrequent adverse events—those occurring in 1/100 to 1/1000 patients; rare—those occurring in fewer than 1/1000 patients.

Blood and Lymphatic System Disorders: Frequent: anemia. Infrequent: lymphadenopathy, leukopenia, neutropenia, iron deficiency anemia, thrombocytopenia.

Cardiac Disorders: Infrequent: bundle branch block right, atrioventricular block first degree.

Metabolic and Nutritional Disorders: Frequent: decreased appetite, increased appetite.

Renal and Urinary Disorders: Frequent: pollakiuria. Infrequent: urinary incontinence, dysuria, hematuria, nephrolithiasis, polyuria, enuresis, nocturia, incontinence.

6.2 Postmarketing Experience

The following adverse reactions have been identified during post approval use of BANZEL. Because these reactions are reported voluntarily from a population of uncertain size, it is not always possible to reliably estimate their frequency or establish a causal relationship to drug exposure.

Dermatologic: Stevens-Johnson syndrome and other serious skin rashes with mucosal involvement.

7 DRUG INTERACTIONS

7.1 Effects of BANZEL on other AEDs

Population pharmacokinetic analysis of average concentration at steady state of carbamazepine, lamotrigine, phenobarbital, phenytoin, topiramate, and valproate showed that typical rufinamide Cavss levels had little effect on the pharmacokinetics of other AEDs. Any effects, when they occur, have been more marked in the pediatric population.

Table 6 summarizes the drug-drug interactions of BANZEL with other AEDs.

Table 6: Summary of drug-drug interactions of BANZEL with other antiepileptic drugs
AED Co-administered | Influence of Rufinamide on AED concentrationa) | Influence of AED on Rufinamide concentration
Carbamazepine | Decrease by 7 to 13%b) | Decrease by 19 to 26% Dependent on dose of carbamazepine
Lamotrigine | Decrease by 7 to 13%b) | No Effect
Phenobarbital | Increase by 8 to 13%b) | Decrease by 25 to 46%c)’ d) Independent of dose or concentration of phenobarbital
Phenytoin | Increase by 7 to 21%b) | Decrease by 25 to 46%c)’ d) Independent of dose or concentration of phenytoin
Topiramate | No Effect | No Effect
Valproate | No Effect | Increase by <16 to 70%c) Dependent on concentration of valproate
Primidone | Not Investigated | Decrease by 25 to 46%c)’ d) Independent of dose or concentration of primidone
Benzodiazepines e) | Not Investigated | No Effect
a) Predictions are based on BANZEL concentrations at the maximum recommended dose of BANZEL.
b) Maximum changes predicted to be in pediatric patients and in adult patients who achieve significantly higher levels of BANZEL, as the effect of rufinamide on these AEDs is concentration-dependent.
c) Larger effects in pediatric patients at high doses/concentrations of AEDs.
d) Phenobarbital, primidone and phenytoin were treated as a single covariate (phenobarbital-type inducers) to examine the effect of these agents on BANZEL clearance.
e) All compounds of the benzodiazepine class were pooled to examine for ‘class effect’ on BANZEL clearance.

Phenytoin: The decrease in clearance of phenytoin estimated at typical levels of rufinamide (Cavss 15 μg/mL) is predicted to increase plasma levels of phenytoin by 7 to 21%. As phenytoin is known to have non-linear pharmacokinetics (clearance becomes saturated at higher doses), it is possible that exposure will be greater than the model prediction.

7.2 Effects of Other AEDs on BANZEL

Potent cytochrome P450 enzyme inducers, such as carbamazepine, phenytoin, primidone, and phenobarbital, appear to increase the clearance of BANZEL (see Table 6). Given that the majority of clearance of BANZEL is via a non-CYP-dependent route, the observed decreases in blood levels seen with carbamazepine, phenytoin, phenobarbital, and primidone are unlikely to be entirely attributable to induction of a P450 enzyme. Other factors explaining this interaction are not understood. Any effects, where they occurred, were likely to be more marked in the pediatric population.

Valproate

Patients stabilized on BANZEL before being prescribed valproate should begin valproate therapy at a low dose, and titrate to a clinically effective dose. Similarly, patients on valproate should begin at a BANZEL dose lower than 10 mg/kg per day (pediatric patients) or 400 mg per day (adults) [see Dosage and Administration (2.5), Clinical Pharmacology (12.3)].

7.3 Effects of BANZEL on Hormonal Contraceptives

Female patients of childbearing age should be warned that the concurrent use of BANZEL with hormonal contraceptives may render this method of contraception less effective. Additional non-hormonal forms of contraception are recommended when using BANZEL [see Use in Specific Populations (8.3), Clinical Pharmacology (12.3) and Patient Counseling Information (17)].

8 USE IN SPECIFIC POPULATIONS

8.1 Pregnancy

Pregnancy Exposure Registry

There is a pregnancy exposure registry that monitors pregnancy outcomes in women exposed to AEDs, such as BANZEL, during pregnancy. Encourage women who are taking BANZEL during pregnancy to enroll in the North American Antiepileptic Drug (NAAED) Pregnancy Registry by calling 1-888-233-2334 or visiting http://www.aedpregnancyregistry.org

Risk Summary

There are no adequate data on the developmental risks associated with use of BANZEL in pregnant women. In animal reproduction studies, oral administration of rufinamide resulted in developmental toxicity in pregnant rats and rabbits at clinically relevant doses [see Data].

In the U.S. general population, the estimated background risk of major birth defects and miscarriage in clinically recognized pregnancies is 2-4% and 15-20%, respectively. The background risk of major birth defects and miscarriage for the indicated population is unknown.

Data

Animal data

Oral administration of rufinamide (0, 20, 100, or 300 mg/kg/day) to pregnant rats throughout organogenesis resulted in decreased fetal weight and increased incidence of fetal skeletal abnormalities at 100 and 300 mg/kg/day, which were associated with maternal toxicity. The maternal plasma exposure (AUC) at the no-adverse effect dose (20 mg/kg/day) for developmental toxicity was less than that in humans at the maximum recommended human dose (MRHD) of 3200 mg/day.

Oral administration of rufinamide (0, 30, 200, or 1000 mg/kg/day) to pregnant rabbits throughout organogenesis resulted in embryofetal death, decreased fetal body weight, and increased incidence of fetal visceral and skeletal abnormalities at doses of 200 and 1000 mg/kg/day. The high dose (1000 mg/kg/day) was associated with abortion. Plasma exposure (AUC) at the no-adverse effect dose (30 mg/kg/day) was less than that in humans at the MRHD.

When rufinamide was orally administered (0, 5, 30, or 150 mg/kg/day) to pregnant rats throughout pregnancy and lactation, decreased offspring growth and survival were observed at all doses tested. A no-effect dose for adverse effects on pre- and postnatal development was not established. At the lowest dose tested (5 mg/kg/day), plasma exposure (AUC) was less than that in humans at the MRHD.

8.2 Lactation

Risk Summary

There are no data on the presence of rufinamide in human milk, the effects on the breastfed infant, or the effects of the drug on milk production.

The developmental and health benefits of breastfeeding should be considered along with the mother’s clinical need for BANZEL and any potential adverse effects on the breastfed infant from BANZEL or from the underlying maternal condition.

8.3 Females and Males of Reproductive Potential

Contraception

Use of BANZEL may reduce the effectiveness of hormonal contraceptives containing ethinyl estradiol or norethindrone. Advise women of reproductive potential taking BANZEL who are using a contraceptive containing ethinyl estradiol and norethindrone to use an additional non-hormonal form of contraception [see Drug Interactions (7.3) and Clinical Pharmacology (12.3)].

Infertility

The effect of rufinamide on fertility in humans has not been established. Oral administration of rufinamide (20, 60, 200, and 600 mg/kg/day) to male and female rats prior to mating, during mating, and during early gestation (females only) resulted in the impairment of fertility at all dose levels tested. The no-effect dose was not established. The plasma exposure level at 20 mg/kg was approximately 0.2 times the human plasma AUC at the MRHD [see Nonclinical Toxicology (13.1)].

8.4 Pediatric Use

Safety and effectiveness have been established in pediatric patients 1 to 17 years of age. The effectiveness of BANZEL in pediatric patients 4 years of age and older was based upon an adequate and well-controlled trial of BANZEL that included both adults and pediatric patients, 4 years of age and older, with Lennox-Gastaut Syndrome. The effectiveness in patients 1 to less than 4 years was based upon a bridging pharmacokinetic and safety study [see Dosage and Administration (2.1), Adverse Reactions (6.1), and Clinical Studies (14)]. The pharmacokinetics of rufinamide in the pediatric patients, ages 1 to less than 4 years of age is similar to children older than 4 years of age and adults [see Clinical Pharmacology (12.3)].

Safety and effectiveness in pediatric patients below the age of 1 year has not been established.

Oral administration of rufinamide (0, 15, 50, or 150 mg/kg) to young rats for 10 weeks starting on postnatal day 7 resulted in decreased brain weights at the mid and high doses and neurobehavioral impairment (learning and memory deficit, altered startle response, decreased locomotor activity) and decreased growth (decreased body weight) at the highest dose tested. The no-effect dose for adverse effects on postnatal development in rats (15 mg/kg) was associated with a plasma exposure (AUC) lower than that in humans at the maximum recommended human dose (MRHD) of 3200 mg/day.

8.5 Geriatric Use

Clinical studies of BANZEL did not include sufficient numbers of subjects aged 65 and over to determine whether they respond differently from younger subjects. In general, dose selection for an elderly patient should be cautious, usually starting at the low end of the dosing range, reflecting the greater frequency of decreased hepatic, renal, or cardiac function, and of concomitant disease or other drug therapy.

Pharmacokinetics of rufinamide in the elderly are similar to that in the young subjects [see Clinical Pharmacology (12.3)].

8.6 Renal Impairment

Rufinamide pharmacokinetics in patients with severe renal impairment (creatinine clearance < 30 mL/min) was similar to that of healthy subjects. Dose adjustment in patients undergoing dialysis should be considered [see Clinical Pharmacology (12.3)].

8.7 Hepatic Impairment

Use of BANZEL in patients with severe hepatic impairment (Child-Pugh score 10 to 15) is not recommended. Caution should be exercised in treating patients with mild (Child-Pugh score 5 to 6) to moderate (Child-Pugh score 7 to 9) hepatic impairment.

10 OVERDOSAGE

Because strategies for the management of overdose are continually evolving, it is advisable to contact a Certified Poison Control Center to determine the latest recommendations for the management of an overdose of any drug.

One overdose of 7200 mg per day BANZEL was reported in an adult during the clinical trials. The overdose was associated with no major signs or symptoms, no medical intervention was required, and the patient continued in the study at the target dose.

Treatment or Management of Overdose: There is no specific antidote for overdose with BANZEL. If clinically indicated, elimination of unabsorbed drug should be attempted by induction of emesis or gastric lavage. Usual precautions should be observed to maintain the airway. General supportive care of the patient is indicated including monitoring of vital signs and observation of the clinical status of the patient.

Hemodialysis: Standard hemodialysis procedures may result in limited clearance of rufinamide. Although there is no experience to date in treating overdose with hemodialysis, the procedure may be considered when indicated by the patient’s clinical state.

11 DESCRIPTION

BANZEL (rufinamide) is a triazole derivative structurally unrelated to currently marketed antiepileptic drugs (AEDs). Rufinamide has the chemical name 1-[(2,6-difluorophenyl)methyl]-1H-1,2,3-triazole-4 carboxamide. It has an empirical formula of C10H8F2N4O and a molecular weight of 238.2. The drug substance is a white, crystalline, odorless, and slightly bitter tasting neutral powder. Rufinamide is practically insoluble in water, slightly soluble in tetrahydrofuran and in methanol, and very slightly soluble in ethanol and in acetonitrile.

BANZEL is available for oral administration in film-coated tablets, scored on both sides, containing 200 and 400 mg of rufinamide. Inactive ingredients are colloidal silicon dioxide, corn starch crosscarmellose sodium, hypromellose, lactose monohydrate, magnesium stearate, microcrystalline cellulose, and sodium lauryl sulphate. The film coating contains hypromellose, iron oxide red, polyethylene glycol, talc, and titanium dioxide.

BANZEL is also available for oral administration as a liquid containing rufinamide at a concentration of 40 mg/mL. Inactive ingredients include microcrystalline cellulose and carboxymethylcellulose sodium, hydroxyethylcellulose, anhydrous citric acid, simethicone emulsion 30%, poloxamer 188, methylparaben, propylparaben, propylene glycol, potassium sorbate, noncrystallizing sorbitol solution 70%, and an orange flavor.

12 CLINICAL PHARMACOLOGY

12.1 Mechanism of Action

The precise mechanism(s) by which rufinamide exerts its antiepileptic effect is unknown.

The results of in vitro studies suggest that the principal mechanism of action of rufinamide is modulation of the activity of sodium channels and, in particular, prolongation of the inactive state of the channel. Rufinamide (≥ 1 μM) significantly slowed sodium channel recovery from inactivation after a prolonged prepulse in cultured cortical neurons, and limited sustained repetitive firing of sodium-dependent action potentials (EC50 of 3.8 μM).

12.3 Pharmacokinetics

Overview

BANZEL oral suspension is bioequivalent on a mg per mg basis to BANZEL tablets. BANZEL is well absorbed after oral administration. However, the rate of absorption is relatively slow and the extent of absorption is decreased as dose is increased. The pharmacokinetics does not change with multiple dosing. Most elimination of rufinamide is via metabolism, with the primary metabolite resulting from enzymatic hydrolysis of the carboxamide moiety to form the carboxylic acid. This metabolic route is not cytochrome P450 dependent. There are no known active metabolites. Plasma half-life of rufinamide is approximately 6-10 hours.

Absorption and Distribution

Following oral administration of BANZEL, peak plasma concentrations occur between 4 and 6 hours (Tmax) both under fed and fasted conditions. BANZEL tablets display decreasing bioavailability with increasing dose after single and multiple dose administration. Based on urinary excretion, the extent of absorption was at least 85% following oral administration of a single dose of 600 mg rufinamide tablet under fed conditions.

Multiple dose pharmacokinetics can be predicted from single dose data for both rufinamide and its metabolite. Given the dosing frequency of every 12 hours and the half-life of 6 to 10 hours, the observed steady-state peak concentration of about two to three times the peak concentration after a single dose is expected.

Food increased the extent of absorption of rufinamide in healthy volunteers by 34% and increased peak exposure by 56% after a single dose of 400 mg tablet, although the Tmax was not elevated [see Dosage and Administration (2.2)].

Only a small fraction of rufinamide (34%) is bound to human serum proteins, predominantly to albumin (27%), giving little risk of displacement drug-drug interactions. Rufinamide was evenly distributed between erythrocytes and plasma. The apparent volume of distribution is dependent upon dose and varies with body surface area. The apparent volume of distribution was about 50 L at 3200 mg per day.

Metabolism

Rufinamide is extensively metabolized but has no active metabolites. Following a radiolabeled dose of rufinamide, less than 2% of the dose was recovered unchanged in urine. The primary biotransformation pathway is carboxylesterase(s) mediated hydrolysis of the carboxamide group to the acid derivative CGP 47292. A few minor additional metabolites were detected in urine, which appeared to be acyl-glucuronides of CGP 47292. There is no involvement of oxidizing cytochrome P450 enzymes or glutathione in the biotransformation process.

Rufinamide is a weak inhibitor of CYP 2E1. It did not show significant inhibition of other CYP enzymes. Rufinamide is a weak inducer of CYP 3A4 enzymes.

Rufinamide did not show any significant inhibition of P-glycoprotein in an in vitro study.

Elimination/Excretion

Renal excretion is the predominant route of elimination for drug related material, accounting for 85% of the dose based on a radiolabeled study. Of the metabolites identified in urine, at least 66% of the rufinamide dose was excreted as the acid metabolite CGP 47292, with 2% of the dose excreted as rufinamide.

The plasma elimination half-life is approximately 6-10 hours in healthy subjects and patients with epilepsy.

Special Populations

Age

- Pediatrics
  Based on a population analysis which included a total of 115 patients, including 85 pediatric patients (24 patients ages 1 to 3 years, 40 patients ages 4 to 11 years, and 21 patients ages 12 to 17 years), the pharmacokinetics of rufinamide was similar across all age groups.
- Elderly
  The results of a study evaluating single-dose (400 mg) and multiple dose (800 mg per day for 6 days) pharmacokinetics of rufinamide in 8 healthy elderly subjects (65-80 years old) and 7 younger healthy subjects (18-45 years old) found no significant age-related differences in the pharmacokinetics of rufinamide.

Sex

Population pharmacokinetic analyses of females show a 6-14% lower apparent clearance of rufinamide compared to males. This effect is not clinically important.

Race

In a population pharmacokinetic analysis of clinical studies, no difference in clearance or volume of distribution of rufinamide was observed between the black and Caucasian subjects, after controlling for body size. Information on other races could not be obtained because of smaller numbers of these subjects.

Renal Impairment

Rufinamide pharmacokinetics in 9 patients with severe renal impairment (creatinine clearance < 30 mL per min) was similar to that of healthy subjects. Patients undergoing dialysis 3 hours post rufinamide dosing showed a reduction in AUC and Cmax by 29% and 16%, respectively.

Drug Interactions

Based on in vitro studies, rufinamide shows little or no inhibition of most cytochrome P450 enzymes at clinically relevant concentrations, with weak inhibition of CYP 2E1. Drugs that are substrates of CYP 2E1 (e.g., chlorzoxazone) may have increased plasma levels in the presence of rufinamide, but this has not been studied.

Based on a population pharmacokinetic analysis, rufinamide clearance was decreased by valproate. In pediatric patients, valproate administration may lead to elevated levels of rufinamide by up to 70% [see Drug Interactions (7.2)].

Based on in vivo drug interaction studies with triazolam and oral contraceptives, rufinamide is a weak inducer of the CYP 3A4 enzyme and can decrease exposure of drugs that are substrates of CYP 3A4.

- Co-administration and pre-treatment of BANZEL (400 mg twice daily) and triazolam resulted in a 37% decrease in AUC and a 23% decrease in Cmax of triazolam, a CYP 3A4 substrate.
- Co-administration of BANZEL (800 mg twice daily for 14 days) and Ortho-Novum 1/35® resulted in a mean decrease in the ethinyl estradiol AUC0-24 of 22% and Cmax by 31% and norethindrone AUC0-24 by 14% and Cmax by 18%, respectively. The clinical significance of this decrease is unknown [see Drug Interactions (7.3) and Use in Specific Populations (8.3)].

Rufinamide is metabolized by carboxylesterases. Drugs that may induce the activity of carboxylesterases may increase the clearance of rufinamide. Broad-spectrum inducers such as carbamazepine and phenobarbital may have minor effects on rufinamide metabolism via this mechanism. Drugs that are inhibitors of carboxylesterases may decrease metabolism of rufinamide.

13 NONCLINICAL TOXICOLOGY

13.1 Carcinogenesis, Mutagenesis, Impairment of Fertility

Carcinogenesis

Rufinamide was given in the diet to mice at 40, 120, and 400 mg/kg per day and to rats at 20, 60, and 200 mg/kg per day for 2 years. The doses in mice were associated with plasma AUCs 0.1 to 1 times the human plasma AUC at the maximum recommended human dose (MRHD, 3200 mg/day). Increased incidences of tumors (benign bone tumors (osteomas) and/or hepatocellular adenomas and carcinomas) were observed in mice at all doses. Increased incidences of thyroid follicular adenomas were observed in rats at all but the low dose; the low dose is < 0.1 times the MRHD on a mg/m^2 basis.

Mutagenesis

Rufinamide was not mutagenic in the in vitro bacterial reverse mutation (Ames) assay or the in vitro mammalian cell point mutation assay. Rufinamide was not clastogenic in the in vitro mammalian cell chromosomal aberration assay or the in vivo rat bone marrow micronucleus assay.

Impairment of Fertility

Oral administration of rufinamide (doses of 20, 60, 200, and 600 mg/kg per day) to male and female rats prior to mating and throughout mating, and continuing in females up to day 6 of gestation resulted in impairment of fertility (decreased conception rates and mating and fertility indices; decreased numbers of corpora lutea, implantations, and live embryos; increased preimplantation loss; decreased sperm count and motility) at all doses tested. Therefore, a no-effect dose was not established. The lowest dose tested was associated with a plasma AUC ≈ 0.2 times the human plasma AUC at the MRHD.

14 CLINICAL STUDIES

Adult and Pediatric Patients ages 4 years and older

The effectiveness of BANZEL as adjunctive treatment for the seizures associated with Lennox-Gastaut Syndrome (LGS) in adult and pediatric patients ages 4 years and older was established in a single multicenter, double-blind, placebo-controlled, randomized, parallel-group study (N=138). Male and female patients (between 4 and 30 years of age) were included if they had a diagnosis of inadequately controlled seizures associated with LGS (including both atypical absence seizures and drop attacks) and were being treated with 1 to 3 concomitant stable dose AEDs. Each patient must have had at least 90 seizures in the month prior to study entry. After completing a 4-week Baseline Phase on stable therapy, patients were randomized to have BANZEL or placebo added to their ongoing therapy during the 12 -week Double-blind Phase. The Double-blind Phase consisted of 2 periods: the Titration Period (1 to 2 weeks) and the Maintenance Period (10 weeks). During the Titration Period, the dose was increased to a target dosage of approximately 45 mg/kg per day (3200 mg in adults of > 70 kg), given on a twice daily schedule. Dosage reductions were permitted during titration if problems in tolerability were encountered. Final doses at titration were to remain stable during the maintenance period. Target dosage was achieved in 88% of the BANZEL-treated patients. The majority of these patients reached the target dose within 7 days, with the remaining patients achieving the target dose within 14 days.

The primary efficacy variables were:

- The percent change in total seizure frequency per 28 days;
- The percent change in tonic-atonic (drop attacks) seizure frequency per 28 days;
- Seizure severity from the Parent/Guardian Global Evaluation of the patient’s condition. This was a 7-point assessment performed at the end of the Double-blind Phase. A score of +3 indicated that the patient’s seizure severity was very much improved, a score of 0 that the seizure severity was unchanged, and a score of -3 that the seizure severity was very much worse.

The results of the three primary endpoints are shown in Table 7 below.

Table 7: Lennox-Gastaut Syndrome Trial Seizure Frequency Primary Efficacy Variable Results
Variable | Placebo | Rufinamide
Median percent change in total seizure frequency per 28 days | -11.7 | -32.7 (p=0.0015)
Median percent change in tonic-atonic seizure frequency per 28 days | 1.4 | -42.5 (p<0.0001)
Improvement in Seizure Severity Rating from Global Evaluation | 30.6 | 53.4 (p=0.0041)

Pediatric Patients ages 1 to less than 4 years

The effectiveness of BANZEL as adjunctive treatment for the seizures associated with Lennox-Gastaut Syndrome in pediatric patients ages 1 year to less than 4 years was established based on a single multi-center, open-label, active-controlled, randomized, pharmacokinetic bridging study. The pharmacokinetic profile of BANZEL is not significantly affected by age either as a continuous covariate (1 to 35 years) or as a categorical covariate (age categories: 1 to less than 4 years and 4 years of age and older), after body weight is taken into consideration.

16 HOW SUPPLIED/STORAGE AND HANDLING

16.1 How Supplied

BANZEL 200 mg tablets (containing 200 mg rufinamide) are pink in color, film-coated, oblong-shape tablets, with a score on both sides, imprinted with “ 262” on one side. They are available in bottles of 120 (NDC 62856-582-52).

BANZEL 400 mg tablets (containing 400 mg rufinamide) are pink in color, film-coated, oblong-shape tablets, with a score on both sides, imprinted with “ 263” on one side. They are available in bottles of 120 (NDC 62856-583-52).

BANZEL oral suspension is an orange flavored liquid supplied in a polyethylene terephthalate (PET) bottle with child-resistant closure. The oral suspension is packaged with a dispenser set which contains a calibrated oral dosing syringe and an adapter. Store the oral suspension in an upright position. Use within 90 days of first opening the bottle, then discard any remainder. The oral suspension is available in bottles of 460 mL (NDC 62856-584-46).

16.2 Storage and Handling

Store the tablets at 25ºC (77ºF); excursions permitted to 15º- 30ºC (59ºF - 86ºF). Protect from moisture. Replace cap securely after opening.

Store the oral suspension at 25ºC (77ºF); excursions permitted to 15º- 30ºC (59ºF - 86ºF). Replace cap securely after opening. The cap fits properly in place when the adapter is in place.

17 PATIENT COUNSELING INFORMATION

Advise the patient to read the FDA-approved patient labeling (Medication Guide and Instructions for Use).

Administration Information

- Advise patients to take BANZEL with food [see Dosage and Administration (2.2)].
- Advise patients who are prescribed the oral suspension to shake the bottle vigorously before every administration and to use the adaptor and oral dosing syringe [see Dosage and Administration (2.2)].

Suicidal Thinking and Behavior

Inform patients, their caregivers, and families that antiepileptic drugs increase the risk of suicidal thoughts and behavior and should be advised of the need to be alert for the emergence or worsening of the signs and symptoms of depression, any unusual changes in mood or behavior, or the emergence of suicidal thoughts, behavior, or thoughts about self-harm. Behaviors of concern should be reported immediately to healthcare providers [see Warnings and Precautions (5.1)].

Central Nervous System Reactions

Inform patients about the potential for somnolence or dizziness and advise them not to drive or operate machinery until they have gained sufficient experience on BANZEL to gauge whether it adversely affects their mental and/or motor performance [see Warnings and Precautions (5.2)].

Multi-Organ Hypersensitivity Reactions

Advise patients to notify their physician if they experience a rash associated with fever [see Warnings and Precautions (5.4)].

Drug Interactions

- Inform female patients of childbearing age that the concurrent use of BANZEL with hormonal contraceptives may render this method of contraception less effective. Recommend patients use additional non-hormonal forms of contraception when using BANZEL [see Drug Interactions (7.3) and Use in Specific Populations (8.3)].
- Inform patients that alcohol in combination with BANZEL may cause additive central nervous system effects.

Pregnancy

Advise patients to notify their physician if they become pregnant or intend to become pregnant during therapy. Encourage patients to enroll in the North American Antiepileptic Drug Pregnancy Registry if they become pregnant. To enroll, patients can call the toll free number 1-888-233-2334 [see Use in Specific Populations (8.1)].

Breast-feeding

Advise patients to notify their physician if they are breast-feeding or intend to breast-feed [see Use in Specific Populations (8.2)].

Medication Guide
BANZEL (ban-‘zel)
[rufinamide]
Tablets and Oral Suspension

Read this Medication Guide before you start taking BANZEL and each time you get a refill. There may be new information. This information does not take the place of talking to your healthcare provider about your medical condition or treatment.

What is the most important information I should know about BANZEL?

Do not stop taking BANZEL without first talking to your healthcare provider.

Stopping BANZEL suddenly can cause serious problems.

BANZEL can cause serious side effects, including:

1. Like other antiepileptic drugs, BANZEL may cause suicidal thoughts or actions in a very small number of people, about 1 in 500.
Call a healthcare provider right away if you have any of these symptoms, especially if they are new, worse, or worry you:

- thoughts about suicide or dying
- attempt to commit suicide
- new or worse depression
- new or worse anxiety
- feeling agitated or restless
- panic attacks
- trouble sleeping (insomnia)
- new or worse irritability
- acting aggressive, being angry, or violent
- acting on dangerous impulses
- an extreme increase in activity and talking (mania)
- other unusual changes in behavior or mood
- Suicidal thoughts or actions can be caused by things other than medicines. If you have suicidal thoughts or actions, your healthcare provider may check for other causes.

How can I watch for early symptoms of suicidal thoughts and actions?

- Pay attention to any changes, especially sudden changes, in mood, behaviors, thoughts, or feelings.
- Keep all follow-up visits with your healthcare provider as scheduled.

Call your healthcare provider between visits as needed, especially if you are worried about symptoms.

Do not stop BANZEL without first talking to a healthcare provider.

- Stopping BANZEL suddenly can cause serious problems. Stopping a seizure medicine suddenly in a patient who has epilepsy can cause seizures that will not stop (status epilepticus).

2. BANZEL may cause you to feel sleepy, tired, weak, dizzy, or have problems with coordination and walking.

What is BANZEL?

BANZEL is a prescription medicine used with other medicines to treat seizures associated with Lennox-Gastaut Syndrome (LGS) in adults and pediatric patients 1 year of age and older.

It is not known if BANZEL is safe and effective in the treatment of Lennox-Gastaut Syndrome in pediatric patients under 1 year of age.

Who should not take BANZEL?

Do not take BANZEL if you have a genetic condition called familial short QT syndrome, a problem that affects the electrical system of the heart.

What should I tell my healthcare provider before taking BANZEL?

Before you take BANZEL, tell your healthcare provider if you:

- have heart problems
- have liver problems
- have any other medical problems
- have or have had suicidal thoughts or actions, depression or mood problems
- are pregnant or plan to become pregnant. It is not known if BANZEL can harm your unborn baby. Tell your healthcare provider right away if you become pregnant while taking BANZEL. You and your healthcare provider will decide if you should take BANZEL while you are pregnant.
- BANZEL may make certain types of birth control less effective. Talk to your healthcare provider about the best birth control methods for you while you take BANZEL.
  ○ If you become pregnant while taking BANZEL, talk to your healthcare provider about registering with the North American Antiepileptic Drug Pregnancy Registry. You can enroll in this registry by calling 1-888-233-2334. The purpose of this registry is to collect information about the safety of antiepileptic medicines during pregnancy.
- are breastfeeding or plan to breastfeed. It is not known if BANZEL will pass into your breast milk. Talk to your healthcare provider about the best way to feed your baby if you take BANZEL.

Tell your healthcare provider about all the medicines you take, including prescription and non-prescription medicines, vitamins, and herbal supplements.

Taking BANZEL with certain other medicines can cause side effects or affect how well they work. Do not start or stop other medicines without talking to your healthcare provider.

Know the medicines you take. Keep a list of them and show it to your healthcare provider and pharmacist each time you get a new medicine.

How should I take BANZEL?

- Take BANZEL exactly as your healthcare provider tells you. Your healthcare provider will tell you how much BANZEL to take.
- Your healthcare provider may change your dose. Do not change your dose of BANZEL without talking to your healthcare provider.
- Take BANZEL with food.
- BANZEL tablets can be swallowed whole, cut in half or crushed.
- If you take BANZEL Oral Suspension instead of BANZEL tablets, shake the bottle well before you take each dose. Measure your dose of BANZEL Oral Suspension using the bottle adapter and dosing syringes provided.
  See the complete Instructions for Use below for information on how to use the dosing syringes and measure your dose of BANZEL Oral Suspension.
- If you take too much BANZEL, call your local Poison Control Center or get emergency medical help right away.

What should I avoid while taking BANZEL?

- Do not drink alcohol or take other medicines that make you sleepy or dizzy while taking BANZEL until you talk to your healthcare provider. BANZEL taken with alcohol or medicines that cause sleepiness or dizziness may make your sleepiness or dizziness worse.
- Do not drive, operate heavy machinery, or do other dangerous activities until you know how BANZEL affects you. BANZEL can slow your thinking and motor skills.

What are the possible side effects of BANZEL?

See “What is the most important information I should know about BANZEL?”

BANZEL may cause serious side effects including:

- BANZEL can also cause allergic reactions or serious problems which may affect organs and other parts of your body like the liver or blood cells. You may or may not have a rash with these types of reactions.

Call your healthcare provider right away if you have any of the following. Symptoms may include:

- swelling of your face, eyes, lips, or tongue
- trouble swallowing or breathing
- a skin rash
- hives
- fever, swollen glands, or sore throat that do not go away or come and go
- swollen glands
- yellowing of your skin or eyes
- dark urine
- unusual bruising or bleeding
- severe fatigue or weakness
- severe muscle pain
- your seizures happen more often or become worse

Call your healthcare provider right away if you have any of the symptoms listed above.

The most common side effects of BANZEL include:

- headache
- dizziness
- tiredness
- sleepiness
- nausea
- vomiting

Tell your healthcare provider about any side effect that bothers you or that does not go away. These are not all of the possible side effects of BANZEL. For more information, ask your healthcare provider or pharmacist.

Call your doctor for medical advice about side effects. You may report side effects to FDA at 1-800-FDA-1088.

How should I store BANZEL?

- Store BANZEL tablets and oral suspension at 59ºF to 86ºF (15ºC to 30ºC).

Tablets

- Keep BANZEL tablets in a dry place.

Oral Suspension

- Replace the cap securely after opening.
- Keep BANZEL Oral Suspension in an upright position.
- Use BANZEL Oral Suspension within 90 days of first opening the bottle.

Keep BANZEL and all medicines out of the reach of children.

General Information about the safe and effective use of BANZEL

Medicines are sometimes prescribed for purposes other than those listed in a Medication Guide. Do not use BANZEL for a condition for which it was not prescribed. Do not give BANZEL to other people, even if they have the same symptoms that you have. It may harm them.

This Medication Guide summarizes the most important information about BANZEL. If you would like more information, talk with your doctor. You can ask your pharmacist or doctor for information about BANZEL that is written for health professionals.

For more information, go to www.banzel.com or call 1-888-274-2378.

What are the ingredients in BANZEL?

Tablets

Active ingredient: rufinamide

Inactive ingredients: colloidal silicon dioxide, corn starch crosscarmellose sodium, hypromellose, lactose monohydrate, magnesium stearate, microcrystalline cellulose, and sodium lauryl sulphate, iron oxide red, polyethylene glycol, talc, and titanium dioxide.

Oral Suspension

Active ingredient: rufinamide

Inactive ingredients: microcrystalline cellulose and carboxymethylcellulose sodium, hydroxyethylcellulose, anhydrous citric acid, simethicone emulsion 30%, poloxamer 188, methylparaben, propylparaben, propylene glycol, potassium sorbate, noncrystallizing sorbitol solution 70%, orange flavor.

The oral suspension does not contain lactose or gluten and is dye-free. The oral suspension does contain carbohydrates.

Distributed by Eisai Inc., Nutley, NJ 07110

Revised: 12/2021

This Medication Guide has been approved by the U.S. Food and Drug Administration.

© 2008-2021 Eisai Inc.

Instructions for Use
BANZEL (ban-‘zel)
[rufinamide]
Oral Suspension

Read the Instructions for Use before using BANZEL Oral Suspension and each time you get a refill. There may be new information. This leaflet does not take the place of talking with the doctor about your medical condition or treatment.

Prepare the BANZEL Oral Suspension dose

You will need the following supplies: See Figure A

- BANZEL Oral Suspension bottle
- Bottle adapter
- Dosing syringe (2 dosing syringes are included in the BANZEL Oral Suspension box)

Figure A

Your total daily dose of BANZEL Oral Suspension is______mL.
Take BANZEL in 2 equally divided doses:
Morning dose = _____mL Evening dose =______mL
Note: The doctor may change your dose, especially when you are first starting BANZEL Oral Suspension.
If your morning and evening doses are more than 20 mL each, measure each dose using either:

- 2 syringes, or
- 1 syringe, taking two steps to draw up the medicine in that same syringe

Step 1. Remove the BANZEL Oral Suspension bottle, bottle adapter, and 2 syringes from the box. See Figure A

Step 2. Shake the bottle well before each use. See Figure B

Figure B

Step 3. Uncap the bottle and insert the bottle adapter into the bottle. See Figure C

Figure C

Once the bottle adapter is installed, it cannot be removed. See Figure D

Figure D

Step 4. Check the morning or evening dose in milliliters (mL) as prescribed by your doctor. Locate this number on the syringe. See Figure E

Figure E

Step 5. Insert the syringe into the upright bottle and push the plunger all the way down. See Figure F

Figure F

Step 6. With the syringe in place, turn the bottle upside down. Pull the plunger to the number of mL needed (the amount of liquid medicine in Step 4). See Figure G

Figure G

Measure the mLs of medicine from the end of the plunger. See Figure H

Figure H

Step 7. If the dose is more than 20 mL, you can either use:

• 2 syringes, or

• 1 syringe, taking two steps to draw up the medicine in that same syringe

For example:

If your dose is 30 mL, draw up 20 mL in the first syringe and the remaining 10 mL in the second syringe.

or

If your dose is 30 mL, draw up 20 mL in the single syringe and squirt the medicine into your mouth, then draw up the remaining 10 mL in that same syringe.

Repeat Steps 4 through 6 when drawing up the remaining dose of medicine, if your dose is more than 20 mL.

Step 8. Remove the syringe from the bottle adapter.

Step 9. Slowly squirt BANZEL directly into the corner of your mouth. If you need 2 syringes for your dose, slowly squirt the medicine from the first syringe into your mouth, then slowly squirt the medicine from the second syringe into your mouth. See Figure I

Figure I

Step 10. Rinse the syringe (or syringes) with tap water after each use. See Figure J

- Fill a cup with water
- Pull back on the plunger and draw the water from the cup into the syringe
- Push on the plunger to release the water into the sink

Figure J

Step 11. Cap the bottle tightly. The cap will fit over the bottle adapter. Store the bottle upright at 59°F to 86°F (15°C to 30°C). See Figure K

Figure K

This Instructions for Use has been approved by the U. S. Food and Drug Administration. Revised: 12/2022

PACKAGE LABEL

PRINCIPAL DISPLAY PANEL

NDC 62856-582-52
BANZEL®
(rufinamide) TABLETS
200 mg
120 tablets

PACKAGE LABEL

PRINCIPAL DISPLAY PANEL

NDC 62856-583-52
BANZEL®
(rufinamide) TABLETS
400 mg
120 tablets

PACKAGE LABEL

PRINCIPAL DISPLAY PANEL

NDC 62856-584-46
BANZEL®
(rufinamide) ORAL SUSPENSION
40 mg/mL
460 mL